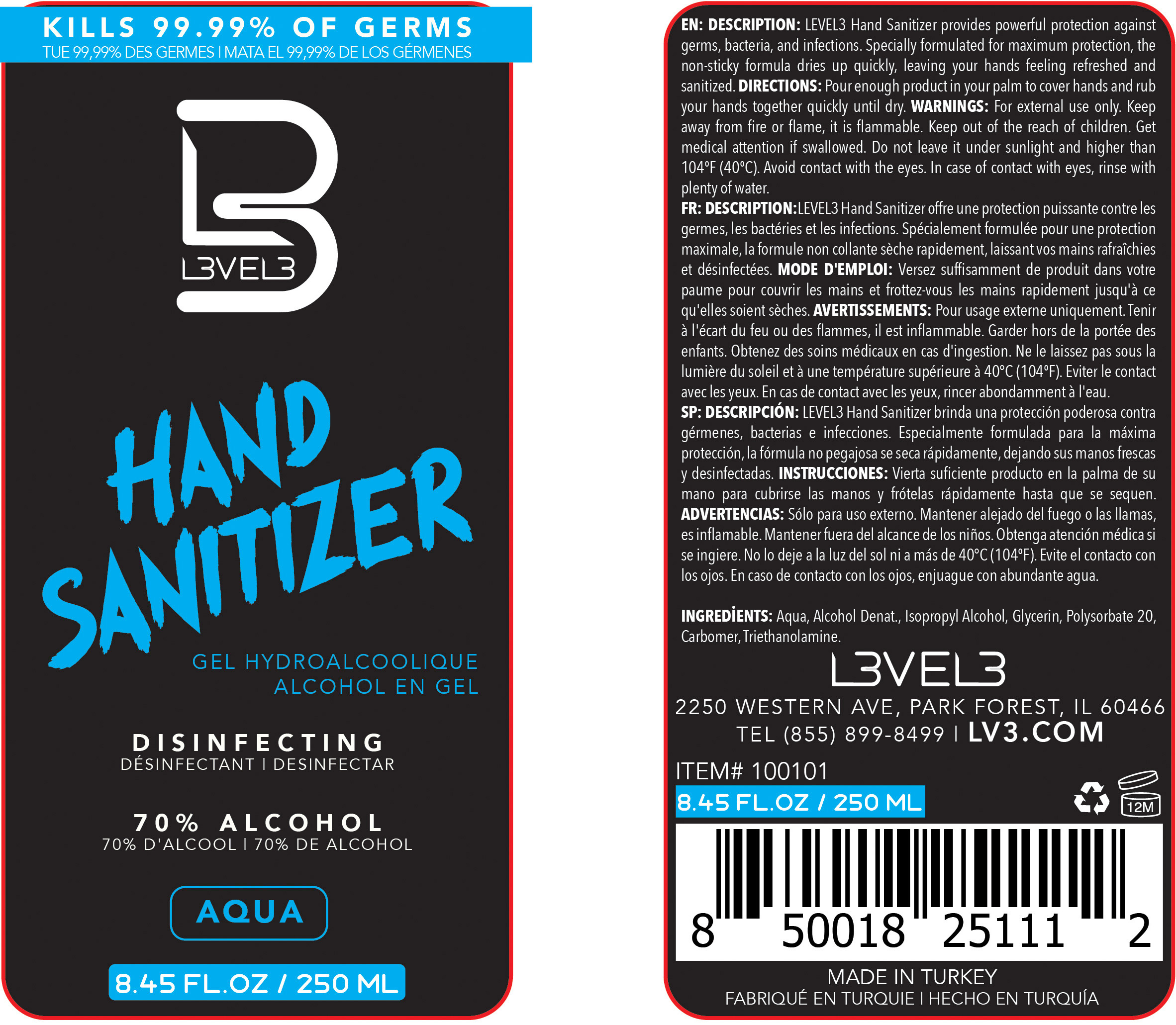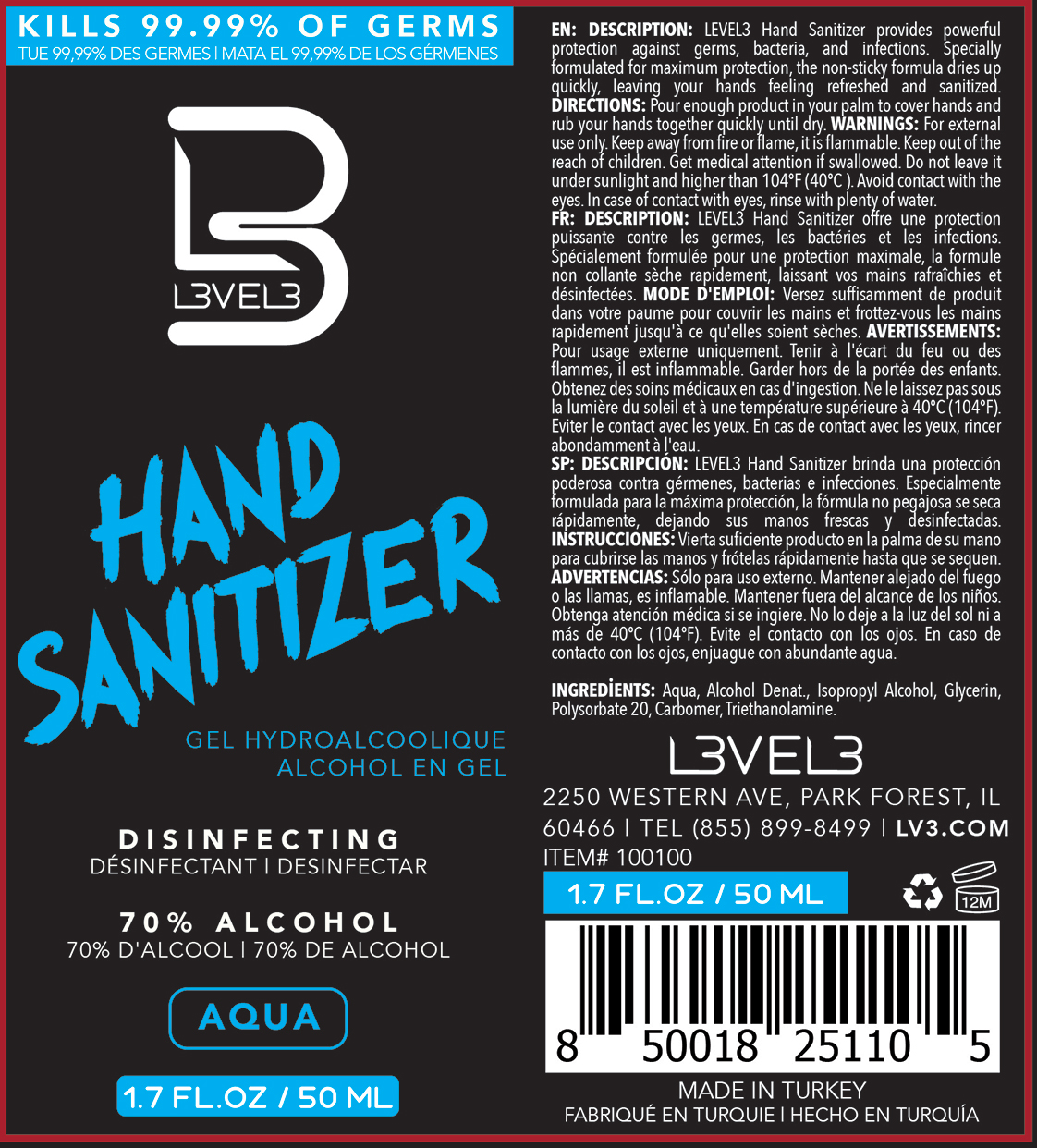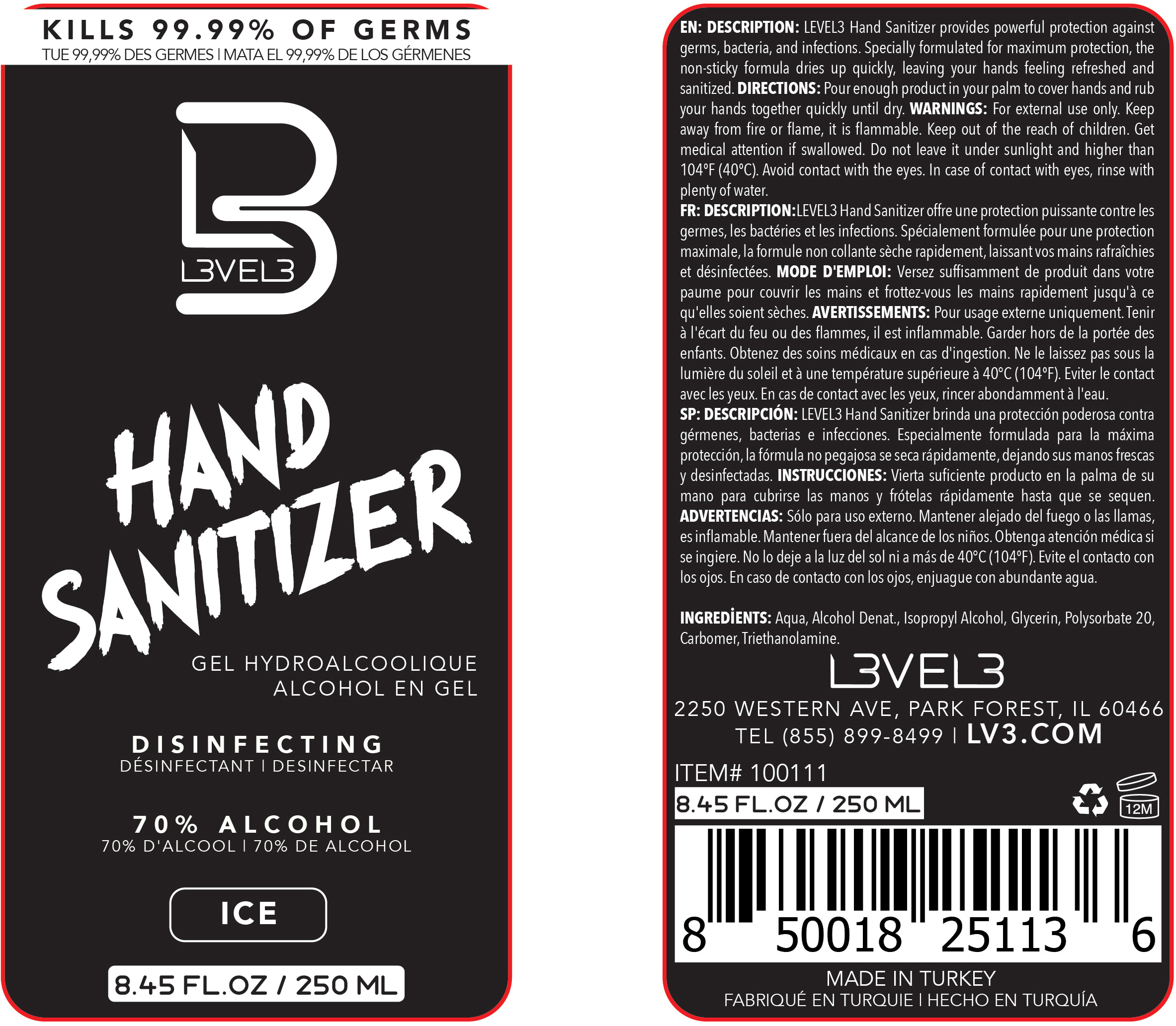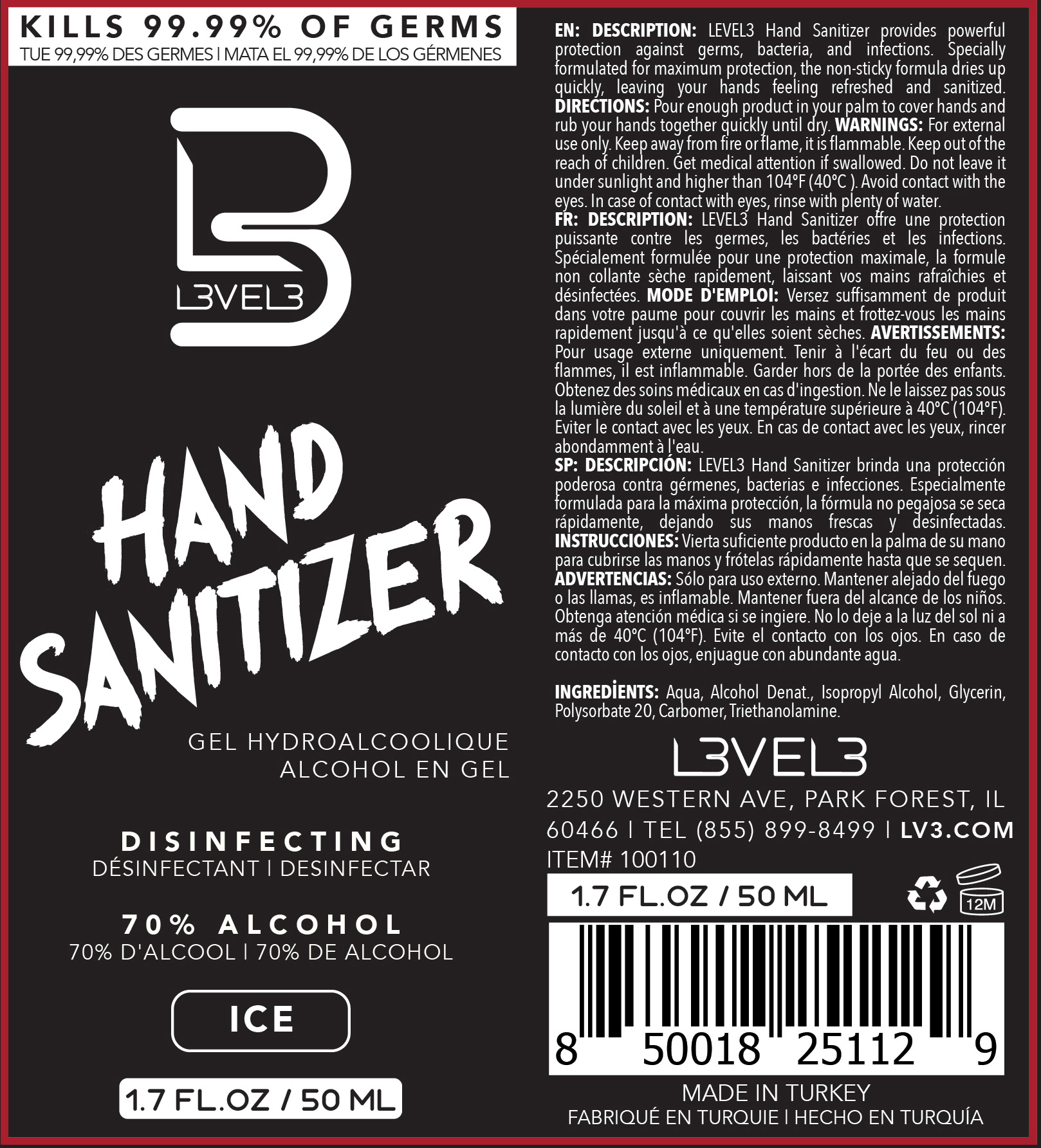 DRUG LABEL: Hand Sanitizer
NDC: 80848-001 | Form: GEL
Manufacturer: L3VEL3 LLC
Category: otc | Type: HUMAN OTC DRUG LABEL
Date: 20201008

ACTIVE INGREDIENTS: ALCOHOL 64 mL/100 mL; ISOPROPYL ALCOHOL 10 mL/100 mL
INACTIVE INGREDIENTS: POLYSORBATE 20 1 mL/100 mL; GLYCERIN 1 mL/100 mL; WATER; TROLAMINE 0.6 mL/100 mL; CARBOXYMETHYLCELLULOSE SODIUM, UNSPECIFIED FORM 0.4 mL/100 mL

Hand Sanitizer

PURPOSE

Hand Sanitizer

DESCRIPTION:

LEVEL3 Hand Sanitizer provides powerful protection against germs, bacteria, and infections. Specially formulated for maximum protection, the non-sticky formula dries up quickly, leaving your hands feeling refreshed and sanitized.

Directions

Pour enough product in your palm to cover hands and rub your hands together quickly until dry.

Warnings

For external use only. Keep away from fire or flame, it is flammable. Keep out of the reach of children. Get medical attention if swallowed. Do not leave it under sunlight and higher than 104ºF (40ºC). Avoid contact with the eyes. In case of contact with eyes, rinse with plenty of water.

Warnings:

Keep out of the reach of children. Get medical attention if swallowed.

Ingredients:

Alcohol Denat, Isopropyl Alcohol.

Ingredients:

Aqua, Glycerin, Polysorbate 20, Carbomer, Triethanolamine.

Package Label - Principal Display Panel

Aqua 50 mL Label NDC: 80848-001-01

Aqua 250 mL Label NDC: 80848-001-02

Ice 50 mL Label NDC: 80848-001-03

Ice 250 mL Label NDC: 80848-001-04